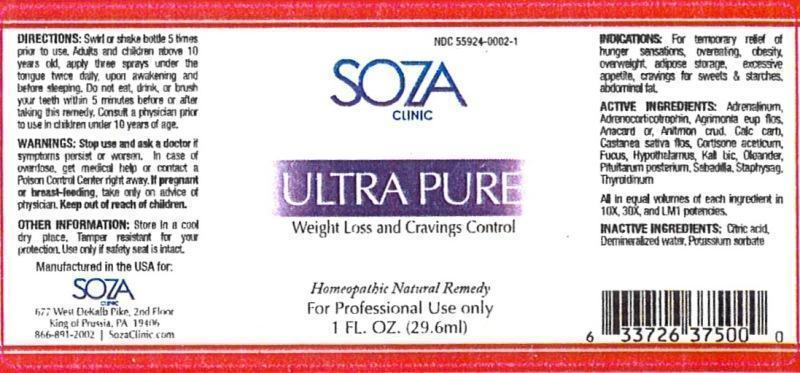 DRUG LABEL: Ultra Pure
NDC: 55924-0002 | Form: LIQUID
Manufacturer: Soza Clinic
Category: homeopathic | Type: HUMAN PRESCRIPTION DRUG LABEL
Date: 20130529

ACTIVE INGREDIENTS: EPINEPHRINE 10 [hp_X]/29.6 mL; CORTICOTROPIN 10 [hp_X]/29.6 mL; AGRIMONIA EUPATORIA FLOWER 10 [hp_X]/29.6 mL; SEMECARPUS ANACARDIUM JUICE 10 [hp_X]/29.6 mL; ANTIMONY TRISULFIDE 10 [hp_X]/29.6 mL; OYSTER SHELL CALCIUM CARBONATE, CRUDE 10 [hp_X]/29.6 mL; CASTANEA SATIVA FLOWER 10 [hp_X]/29.6 mL; CORTISONE ACETATE 10 [hp_X]/29.6 mL; FUCUS VESICULOSUS 10 [hp_X]/29.6 mL; BOS TAURUS HYPOTHALAMUS 10 [hp_X]/29.6 mL; POTASSIUM DICHROMATE 10 [hp_X]/29.6 mL; NERIUM OLEANDER LEAF 10 [hp_X]/29.6 mL; SUS SCROFA PITUITARY GLAND 10 [hp_X]/29.6 mL; SCHOENOCAULON OFFICINALE SEED 10 [hp_X]/29.6 mL; DELPHINIUM STAPHISAGRIA SEED 10 [hp_X]/29.6 mL; THYROID, UNSPECIFIED 10 [hp_X]/29.6 mL
INACTIVE INGREDIENTS: CITRIC ACID MONOHYDRATE; WATER; POTASSIUM SORBATE

Ultra Pure

DOSAGE AND ADMINISTRATION

Directions: Swirl or shake bottle 5 times prior to use. Adults and children above 10 years old, apply three sprays under the tongue twice daily, upon awakening and before sleeping. Do not eat, drink, or brush your teeth within 5 minutes before or after taking this remedy. Consult a physician prior to use in children under 10 years of age.

WARNINGS AND PRECAUTIONS

Warnings: Stop use and ask a doctor if symptoms persist or worsen. In case of overdose, get medical help or contact a Poison Control Center right away. If pregnant or breast-feeding, take only on advice of physician.

Other Information: Store in a cool dry place. Tamper resistant for your protection. Use only if safety seal is intact.

Keep out of reach of children.

INDICATIONS AND USAGE

Indications: For temporary relief of hunger sensations, overeating, obesity, overweight, adipose storage, excessive appetite, cravings for sweets & starches, abdominal fat.

Active Ingredient: Adrenalinum, Adrenocorticotrophin, Agrimonia eupatoria, flos, Anacardium orientale, Antimonium crudum, Calcarea carbonica, Castanea sativa, flos, Cortisone aceticum, Fucus vesiculosus, Hypothalamus, Kali bichromicum, Oleander, Pituitarum posterium, Sabadilla, Staphysagria, Thyroidinum. All in equal volumes of each ingredient in 10X, 30X and LM1 potencies.

INACTIVE INGREDIENT

Inactive ingredients: Citric acid, Demineralized water, Potassium sorbate.

PURPOSE

Indications

For temporary relief of:

- hunger sensations
- overeating
- obesity
- overweight
- adipose storage
- excessive appetite
- cravings for sweets & starches
- abdominal fat